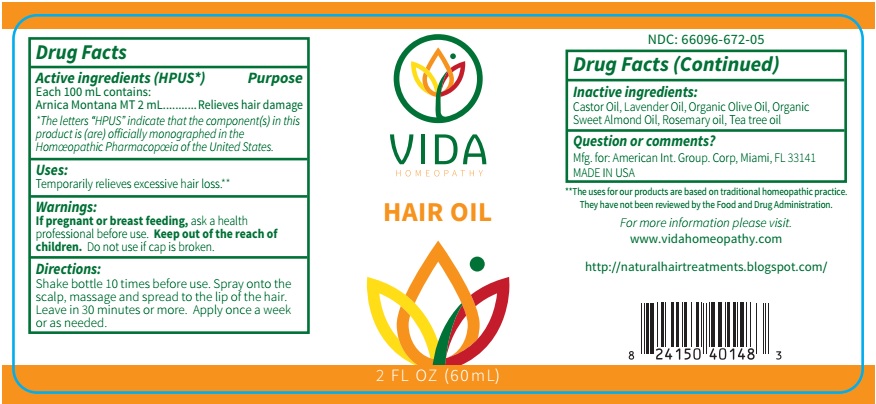 DRUG LABEL: Vida Hair Oil
NDC: 66096-672 | Form: SPRAY
Manufacturer: OHM PHARMA INC.
Category: homeopathic | Type: HUMAN OTC DRUG LABEL
Date: 20190905

ACTIVE INGREDIENTS: ARNICA MONTANA 1 [hp_X]/60 mL
INACTIVE INGREDIENTS: CASTOR OIL; LAVENDER OIL; OLIVE OIL; ALMOND OIL; ROSEMARY OIL; TEA TREE OIL

Vida Hair Oil

Active ingredients (HPUS*) Purpose

Each 100 mL contains:

Arnica Montana MT 2 mL......................Relieves hair damage

*The letters *HPUS* indicate that the component(s) in this product is (are) officially monographed in the Homeopathic Pharmacopeia of the United States.

INDICATIONS AND USAGE

Uses: Temporarily relieves excessive hair loss.**

**The uses for our products are based on traditional homeopathic practice. They have not been reviewed by the Food and Drug Administration.

WARNINGS

Warnings: If pregnant or breast feeding, ask a health professional before use.

- KEEP OUT OF THE REACH OF CHILDREN.

DOSAGE AND ADMINISTRATION

Directions: Shake bottle 10 times before use. Spray onto the scalp, massage and spread to the lip of the hair. Leave in 30 minutes or more. Apply once a week or as needed.

Do not use if cap is broken.

INACTIVE INGREDIENT

Inactive ingredients: Castor Oil, Lavender Oil, Organic Olive Oil, Organic Sweet Almond Oil, Rosemary Oil, Tea Tree Oil.

QUESTIONS

Question or comments? Mfg. for : American Int. Group. Corp, Miami, FL 33141

MADE IN USA

For more information please visit. www.vidahomeopathy.com

http://naturalhairtreatments.blogspot.com/

PACKAGE LABEL

NDC: 66096-672-05

VIDA HOMEOPATHY

HAIR OIL

2 FL OZ (60mL)

PURPOSE

Relieves excessive hair loss.